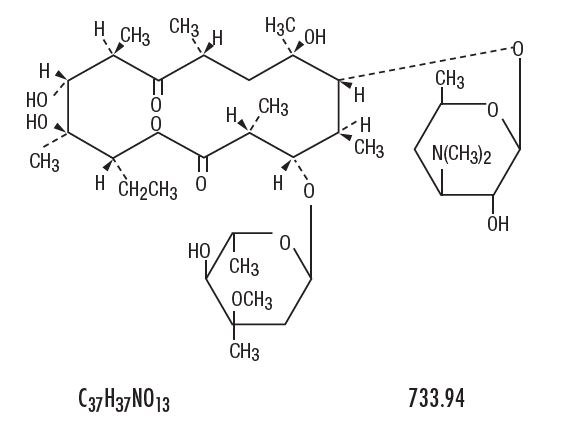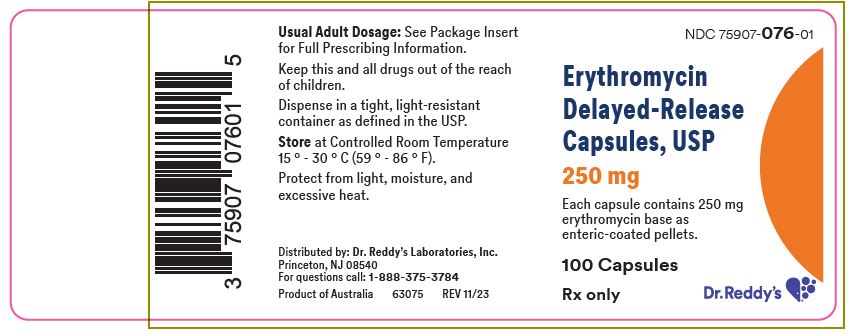 DRUG LABEL: erythromycin
NDC: 75907-076 | Form: CAPSULE, DELAYED RELEASE PELLETS
Manufacturer: Dr. Reddy's Labratories Inc.
Category: prescription | Type: HUMAN PRESCRIPTION DRUG LABEL
Date: 20250925

ACTIVE INGREDIENTS: erythromycin 250 mg/1 1
INACTIVE INGREDIENTS: lactose, unspecified form; povidone, unspecified; FD&C Yellow NO. 6; gelatin, unspecified; titanium dioxide

Erythromycin Delayed-Release Capsules, USP

FULL PRESCRIBING INFORMATION

To reduce the development of drug-resistant bacteria and maintain the effectiveness of erythromycin delayed-release capsules, USP and other antibacterial drugs, erythromycin delayed-release capsules, USP should be used only to treat or prevent infections that are proven or strongly suspected to be caused by bacteria.

DESCRIPTION

Erythromycin delayed-release capsules, USP capsules contain enteric-coated pellets of erythromycin base for oral administration. Each erythromycin delayed-release capsules, USP contains 250 mg of erythromycin base. Also contains: lactose NF, povidone USP, and other ingredients. The capsule shell contains gelatin NF, titanium dioxide USP, FD&C Yellow #6, D&C Yellow #10 and FD&C Red #3.

Erythromycin is produced by a strain of Saccharopolyspora erythraea (formerly Streptomyces erythraeus) and belongs to the macrolide group of antibiotics. It is basic and readily forms salts with acids but it is the base which is microbiologically active. Erythromycin base is (3R *, 4S *, 5S *, 6R *, 7R *, 9R *, 11R *, 12R *, 13S *, 14R *)-4-[(2,6-Dideoxy-3-C-methyl- 3-O-methyl-α-L-ribo-hexopyranosyl)oxy]-14-ethyl-7,12,13-trihydroxy-3,5,7,9,11,13-hexamethyl-6-[[3,4,6- trideoxy-3-(dimethylamino)-β-D-xylo-hexopyranosyl]oxy]-oxacyclo-tetradecane-2,10-dione.

ERYTHROMYCIN

CLINICAL PHARMACOLOGY

Orally administered erythromycin base and its salts are readily absorbed in the microbiologically active form. Interindividual variations in the absorption of erythromycin are, however, observed, and some patients do not achieve acceptable serum levels. Erythromycin is largely bound to plasma proteins, and the freely dissociating bound fraction after administration of erythromycin base represents 90 percent of the total erythromycin absorbed. After absorption, erythromycin diffuses readily into most body fluids. In the absence of meningeal inflammation, low concentrations are normally achieved in the spinal fluid, but the passage of the drug across the blood-brain barrier increases in meningitis. The drug is excreted in human milk. The drug crosses the placental barrier, but fetal plasma levels are low. Erythromycin is not removed by peritoneal dialysis or hemodialysis.

In the presence of normal hepatic function erythromycin is concentrated in the liver and is excreted in the bile; the effect of hepatic dysfunction on biliary excretion of erythromycin is not known. After oral administration, less than 5 percent of the administered dose can be recovered in the active form in the urine.

The enteric coating of pellets in erythromycin delayed-release capsules, USP protects the erythromycin base from inactivation by gastric acidity. Because of their small size and enteric coating, the pellets readily pass intact from the stomach to the small intestine and dissolve efficiently to allow absorption of erythromycin in a uniform manner. After administration of a single dose of a 250 mg erythromycin delayed-release capsule, USP, peak serum levels in the range of 1.13 to 1.68 mcg/mL are attained in approximately 3 hours and decline to 0.30 to 0.42 mcg/mL in 6 hours. Optimal conditions for stability in the presence of gastric secretion and for complete absorption are attained when erythromycin is taken on an empty stomach.

Microbiology

Mechanism of Action

Erythromycin acts by inhibition of protein synthesis by binding 50 S ribosomal subunits of susceptible organisms. It does not affect nucleic acid synthesis.

Resistance

The major route of resistance is modification of the 23S rRNA in the 50S ribosomal subunit to insensitivity, while efflux can also be significant.

Interactions With Other Antimicrobials

Antagonism exists in vitro between erythromycin and clindamycin, lincomycin, and chloramphenicol.

Erythromycin has been shown to be active against most isolates of the following bacteria both in vitro and in clinical infections as described in the INDICATIONS AND USAGE section.

Gram-positive bacteria:

Corynebacterium diphtheriae
Corynebacterium minutissimum
Listeria monocytogenes
Staphylococcus aureus
Streptococcus pneumoniae
Streptococcus pyogenes

Gram-negative bacteria:

Bordetella pertussis
Haemophilus influenzae
Legionella pneumophila
Neisseria gonorrhoeae

Other Microorganisms:

Chlamydia trachomatis
Entamoeba histolytica
Mycoplasma pneumoniae
Treponema pallidum
Ureaplasma urealyticum

Susceptibility Testing

For specific information regarding susceptibility test interpretive criteria, and associated test methods and quality control standards recognized by FDA for this drug, please see: http://www.fda.gov/STIC.

INDICATIONS AND USAGE

Erythromycin is indicated in the treatment of infections caused by susceptible strains of the designated organisms in the diseases listed below:

Upper respiratory tract infections of mild to moderate degree caused by Streptococcus pyogenes, Streptococcus pneumoniae, or Haemophilus influenzae (when used concomitantly with adequate doses of sulfonamides, since many strains of H. influenzae are not susceptible to the erythromycin concentrations ordinarily achieved) (see appropriate sulfonamide labeling for prescribing information).

Lower respiratory tract infections of mild to moderate severity caused by Streptococcus pneumoniae or Streptococcus pyogenes.

Listeriosis caused by Listeria monocytogenes.

Pertussis (whooping cough) caused by Bordetella pertussis. Erythromycin is effective in eliminating the organism from the nasopharynx of infected individuals rendering them noninfectious. Some clinical studies suggest that erythromycin may be helpful in the prophylaxis of pertussis in exposed susceptible individuals.

Respiratory tract infections due to Mycoplasma pneumoniae.

Skin and skin structure infections of mild to moderate severity caused by Streptococcus pyogenes or Staphylococcus aureus (resistant staphylococci may emerge during treatment).

Diphtheria: Infections due to Corynebacterium diphtheriae, as an adjunct to antitoxin, to prevent establishment of carriers and to eradicate the organism in carriers.

Erythrasma: In the treatment of infections due to Corynebacterium minutissimum.

Syphilis caused by Treponema pallidum: Erythromycin is an alternate choice of treatment for primary syphilis in penicillin-allergic patients. In primary syphilis, spinal fluid examinations should be done before treatment and as part of follow-up after therapy.

Intestinal amebiasis caused by Entamoeba histolytica (oral erythromycins only). Extraenteric amebiasis requires treatment with other agents.

Acute pelvic inflammatory disease caused by Neisseria gonorrhoeae: Erythromycin lactobionate for injection, USP followed by erythromycin base orally, as an alternative drug in treatment of acute pelvic inflammatory disease caused by N. gonorrhoeae in female patients with a history of sensitivity to penicillin. Patients should have a serologic test for syphilis before receiving erythromycin as treatment of gonorrhea and a follow-up serologic test for syphilis after 3 months.

Erythromycins are indicated for the treatment of the following infections caused by Chlamydia trachomatis: conjunctivitis of the newborn, pneumonia of infancy, and urogenital infections during pregnancy. When tetracyclines are contraindicated or not tolerated, erythromycin is indicated for the treatment of uncomplicated urethral, endocervical, or rectal infections in adults due to Chlamydia trachomatis.

When tetracyclines are contraindicated or not tolerated, erythromycin is indicated for the treatment of nongonococcal urethritis caused by Ureaplasma urealyticum.

Legionnaires' Disease caused by Legionella pneumophila. Although no controlled clinical efficacy studies have been conducted, in vitro and limited preliminary clinical data suggest that erythromycin may be effective in treating Legionnaires' Disease.

Prophylaxis

Prevention of Initial Attacks of Rheumatic Fever

Penicillin is considered by the American Heart Association to be the drug of choice in the prevention of initial attacks of rheumatic fever (treatment of Streptococcus pyogenes infections of the upper respiratory tract, e.g., tonsillitis or pharyngitis). Erythromycin is indicated for the treatment of penicillin-allergic patients.^1 The therapeutic dose should be administered for ten days.

Prevention of Recurrent Attacks of Rheumatic Fever

Penicillin or sulfonamides are considered by the American Heart Association to be the drugs of choice in the prevention of recurrent attacks of rheumatic fever. In patients who are allergic to penicillin and sulfonamides, oral erythromycin is recommended by the American Heart Association in the long-term prophylaxis of streptococcal pharyngitis (for the prevention of recurrent attacks of rheumatic fever).^1

To reduce the development of drug-resistant bacteria and maintain the effectiveness of erythromycin delayed-release capsules, USP and other antibacterial drugs, erythromycin delayed-release capsules, USP should be used only to treat or prevent infections that are proven or strongly suspected to be caused by susceptible bacteria. When culture and susceptibility information are available, they should be considered in selecting or modifying antibacterial therapy. In the absence of such data, local epidemiology and susceptibility patterns may contribute to the empiric selection of therapy.

CONTRAINDICATIONS

Erythromycin is contraindicated in patients with known hypersensitivity to this antibiotic.

Erythromycin is contraindicated in patients taking terfenadine, astemizole, cisapride, pimozide, ergotamine, or dihydroergotamine (see PRECAUTIONS - Drug Interactions).

Do not use erythromycin concomitantly with HMG CoA reductase inhibitors (statins) that are extensively metabolized by CYP 3A4 (lovastatin or simvastatin), due to the increased risk of myopathy, including rhabdomyolysis (see PRECAUTIONS - Drug Interactions).

WARNINGS

Hepatotoxicity

There have been reports of hepatic dysfunction, including increased liver enzymes, and hepatocellular and/or cholestatic hepatitis, with or without jaundice, occurring in patients receiving oral erythromycin products.

QT Prolongation

Erythromycin has been associated with prolongation of the QT interval and infrequent cases of arrhythmia. Cases of torsades de pointes have been spontaneously reported during postmarketing surveillance in patients receiving erythromycin. Fatalities have been reported. Erythromycin should be avoided in patients with known prolongation of the QT interval, patients with ongoing proarrhythmic conditions such as uncorrected hypokalemia or hypomagnesemia, clinically significant bradycardia, and in patients receiving Class IA (quinidine, procainamide) or Class III (dofetilide, amiodarone, sotalol) antiarrhythmic agents. Elderly patients may be more susceptible to drug-associated effects on the QT interval.

Syphilis in pregnancy

There have been reports suggesting that erythromycin does not reach the fetus in adequate concentration to prevent congenital syphilis. Infants born to women treated during pregnancy with oral erythromycin for early syphilis should be treated with an appropriate penicillin regimen.

Clostridium difficile-associated diarrhea (CDAD) has been reported with use of nearly all antibacterial agents, including erythromycin delayed-release capsules, USP, and may range in severity from mild diarrhea to fatal colitis. Treatment with antibacterial agents alters the normal flora of the colon leading to overgrowth of C. difficile.

C. difficile produces toxins A and B which contribute to the development of CDAD. Hypertoxin producing strains of C. difficile cause increased morbidity and mortality, as these infections can be refractory to antimicrobial therapy and may require colectomy. CDAD must be considered in all patients who present with diarrhea following antibiotic use. Careful medical history is necessary since CDAD has been reported to occur over two months after the administration of antibacterial agents.

If CDAD is suspected or confirmed, ongoing antibiotic use not directed against C. difficile may need to be discontinued. Appropriate fluid and electrolyte management, protein supplementation, antibiotic treatment of C. difficile, and surgical evaluation should be instituted as clinically indicated.

Drug Interactions

Serious adverse reactions have been reported in patients taking erythromycin concomitantly with CYP3A4 substrates. These include colchicine toxicity with colchicine; rhabdomyolysis with simvastatin, lovastatin, and atorvastatin; and hypotension with calcium channel blockers metabolized by CYP3A4 (for example, verapamil, amlodipine, diltiazem) (see PRECAUTIONS, Drug Interactions).

There have been post-marketing reports of colchicine toxicity with concomitant use of erythromycin and colchicine. This interaction is potentially life-threatening, and may occur while using both drugs at their recommended doses (see PRECAUTIONS, Drug Interactions).

Rhabdomyolysis with or without renal impairment has been reported in seriously ill patients receiving erythromycin concomitantly with lovastatin. Therefore, patients receiving concomitant lovastatin and erythromycin should be carefully monitored for creatine kinase (CK) and serum transaminase levels. (See package insert for lovastatin.)

PRECAUTIONS

General

Prescribing erythromycin delayed-release capsules, USP in the absence of a proven or strongly suspected bacterial infection or a prophylactic indication is unlikely to provide benefit to the patient and increases the risk of the development of drug-resistant bacteria.

Since erythromycin is principally excreted by the liver, caution should be exercised when erythromycin is administered to patients with impaired hepatic function (see CLINICAL PHARMACOLOGY and WARNINGS.)

Exacerbation of symptoms of myasthenia gravis and new onset of symptoms of myasthenic syndrome has been reported in patients receiving erythromycin therapy.

There have been reports of infantile hypertrophic pyloric stenosis (IHPS) occurring in infants following erythromycin therapy. In one cohort of 157 newborns who were given erythromycin for pertussis prophylaxis, seven neonates (5 percent) developed symptoms of non bilious vomiting or irritability with feeding and were subsequently diagnosed as having IHPS requiring surgical pyloromyotomy. A possible dose-response effect was described with an absolute risk of IHPS of 5.1 percent for infants who took erythromycin for 8 to 14 days and 10 percent for infants who took erythromycin for 15 to 21 days.^2 Since erythromycin may be used in the treatment of conditions in infants which are associated with significant mortality or morbidity (such as pertussis or neonatal Chlamydia trachomatis infections), the benefit of erythromycin therapy needs to be weighed against the potential risk of developing IHPS. Parents should be informed to contact their physician if vomiting or irritability with feeding occurs.

Prolonged or repeated use of erythromycin may result in an overgrowth of nonsusceptible bacteria or fungi. If superinfection occurs, erythromycin should be discontinued and appropriate therapy instituted.

When indicated, incision and drainage or other surgical procedures should be performed in conjunction with antibiotic therapy.

Information for Patients

Patients should be counseled that antibacterial drugs including erythromycin delayed-release capsules, USP should only be used to treat bacterial infections. They do not treat viral infections (for example, the common cold). When erythromycin delayed-release capsules, USP are prescribed to treat a bacterial infection, patients should be told that although it is common to feel better early in the course of therapy, the medication should be taken exactly as directed. Skipping doses or not completing the full course of therapy may (1) decrease the effectiveness of the immediate treatment and (2) increase the likelihood that bacteria will develop resistance and will not be treatable by erythromycin delayed-release capsules, USP or other antibacterial drugs in the future.

Diarrhea is a common problem caused by antibiotics which usually ends when the antibiotic is discontinued. Sometimes after starting treatment with antibiotics, patients can develop watery and bloody stools (with or without stomach cramps and fever) even as late as two or more months after having taken the last dose of the antibiotic. If this occurs, patients should contact their physician as soon as possible.

Drug Interactions

Theophylline

Erythromycin use in patients who are receiving high doses of theophylline may be associated with an increase in serum theophylline levels and potential theophylline toxicity. In case of theophylline toxicity and/or elevated serum theophylline levels, the dose of theophylline should be reduced while the patient is receiving concomitant erythromycin therapy.

There have been published reports suggesting that when oral erythromycin is given concurrently with theophylline there is a significant decrease in erythromycin serum concentrations of approximately 35 percent. The mechanism by which this interaction occurs is unknown. The decrease in erythromycin concentrations due to co-administration of theophylline could result in subtherapeutic concentrations of erythromycin.

Hypotension, bradyarrhythmias, and lactic acidosis have been observed in patients receiving concurrent verapamil, belonging to the calcium channel blockers drug class.

Concomitant administration of erythromycin and digoxin has been reported to result in elevated digoxin serum levels.

There have been reports of increased anticoagulant effects when erythromycin and oral anticoagulants were used concomitantly. Increased anticoagulation effects due to interactions of erythromycin with oral anticoagulants may be more pronounced in the elderly.

Erythromycin is a substrate and inhibitor of the 3A isoform subfamily of the cytochrome P450 enzyme system (CYP3A). Co-administration of erythromycin and a drug primarily metabolized by CYP3A may be associated with elevations in drug concentrations that could increase or prolong both the therapeutic and adverse effects of the concomitant drug. Dosage adjustments may be considered, and when possible, serum concentrations of drugs primarily metabolized by CYP3A should be monitored closely in patients concurrently receiving erythromycin.

The following are examples of some clinically significant CYP3A based drug interactions. Interactions with other drugs metabolized by the CYP3A isoform are also possible. The following CYP3A based drug interactions have been observed with erythromycin products in post-marketing experience:

Ergotamine/dihydroergotamine

Post-marketing reports indicate that co-administration of erythromycin with ergotamine or dihydroergotamine has been associated with acute ergot toxicity characterized by vasospasm and ischemia of the extremities and other tissues including central nervous system. Concomitant administration of erythromycin with ergotamine or dihydroergotamine is contraindicated (see CONTRAINDICATIONS).

Triazolobenzodiazepines (such as triazolam and alprazolam) and related benzodiazepines

Erythromycin has been reported to decrease the clearance of triazolam and midazolam, and thus, may increase the pharmacologic effect of these benzodiazepines.

HMG-CoA Reductase Inhibitors

Erythromycin has been reported to increase concentrations of HMG-CoA reductase inhibitors (for example, lovastatin and simvastatin). Rare reports of rhabdomyolysis have been reported in patients taking these drugs concomitantly (see CONTRAINDICATIONS).

Sildenafil (Viagra)

Erythromycin has been reported to increase the systemic exposure (AUC) of sildenafil. Reduction of sildenafil dosage should be considered. (See Viagra package insert.)

There have been spontaneous or published reports of CYP3A based interactions of erythromycin with carbamazepine, cyclosporine, tacrolimus, alfentanil, disopyramide, bromocriptine, rifabutin, quinidine methylprednisolone, cilostazol, and vinblastine.

Concomitant administration of erythromycin with cisapride, pimozide, astemizole, or terfenadine is contraindicated (see CONTRAINDICATIONS).

In addition, there have been reports of interactions of erythromycin with drugs not thought to be metabolized by CYP3A, including hexobarbital, phenytoin, and valproate.

Erythromycin has been reported to significantly alter the metabolism of the nonsedating antihistamines terfenadine and astemizole when taken concomitantly. Rare cases of serious cardiovascular adverse events, including electrocardiographic QT/QTc interval prolongation, cardiac arrest, torsades de pointes, and other ventricular arrhythmias, have been observed (see CONTRAINDICATIONS). In addition, deaths have been reported rarely with concomitant administration of terfenadine and erythromycin.

There have been post-marketing reports of drug interactions when erythromycin was co-administered with cisapride, resulting in QT prolongation, cardiac arrhythmias, ventricular tachycardia, ventricular fibrillation, and torsades de pointes, most likely due to the inhibition of hepatic metabolism of cisapride by erythromycin. Fatalities have been reported (see CONTRAINDICATIONS).

Colchicine

Colchicine is a substrate for both CYP3A4 and the efflux transporter P-glycoprotein (P-gp). Erythromycin is considered a moderate inhibitor of CYP3A4. A significant increase in colchicine plasma concentration is anticipated when co-administered with moderate CYP3A4 inhibitors such as erythromycin. If co-administration of colchicine and erythromycin is necessary, the starting dose of colchicine may need to be reduced, and the maximum colchicine dose should be lowered. Patients should be monitored for clinical symptoms of colchicine toxicity (see WARNINGS).

Drug/Laboratory test interactions

Erythromycin interferes with the fluorometric determination of urinary catecholamines.

Carcinogenesis, Mutagenesis and Impairment of Fertility

Long-term (2-year) oral studies conducted in rats with erythromycin base did not provide evidence of tumorigenicity. Mutagenicity studies have not been conducted. There was no apparent effect on male or female fertility in rats fed erythromycin (base) at levels up to 0.25 percent of diet.

Pregnancy

Teratogenic Effects

There was no evidence of teratogenicity or any other adverse effect on reproduction in female rats fed erythromycin base (up to 0.25 percent of diet) prior to and during mating, during gestation, and through weaning of two successive litters. There are, however, no adequate and well-controlled studies in pregnant women. Because animal reproduction studies are not always predictive of human response, this drug should be used during pregnancy only if clearly needed.

Labor and Delivery

The effect of erythromycin on labor and delivery is unknown.

Nursing Mothers

Erythromycin is excreted in human milk. Caution should be exercised when erythromycin is administered to a nursing woman.

Pediatric Use

See INDICATIONS AND USAGE and DOSAGE AND ADMINISTRATION.

Geriatric Use

Clinical studies with erythromycin delayed-release capsules, USP did not include sufficient numbers of subjects aged 65 and over to determine whether they respond differently from younger subjects. Other reported clinical experience has not identified differences in responses between the elderly and younger patients. In general, dose selection for an elderly patient should be cautious, usually starting at the low end of the dosing range, reflecting the greater frequency of the decreased hepatic, renal, or cardiac function, and of concomitant disease or other drug therapy.

Elderly patients may be more susceptible to development of torsades de pointes arrhythmias than younger patients (see WARNINGS).

Elderly patients may experience increased effects of oral anticoagulant therapy while undergoing treatment with erythromycin (see PRECAUTIONS, Drug Interactions.)

erythromycin delayed-release capsules, USP do not contain sodium.

ADVERSE REACTIONS

The most frequent side effects of oral erythromycin preparations are gastrointestinal and are dose-related. They include nausea, vomiting, abdominal pain, diarrhea and anorexia. Symptoms of hepatitis, hepatic dysfunction and/or abnormal liver function test results may occur (see WARNINGS).

Onset of pseudomembranous colitis symptoms may occur during or after antibacterial treatment (see WARNINGS).

Erythromycin has been associated with QT prolongation and ventricular arrhythmias, including ventricular tachycardia and torsade de pointes (see WARNINGS).

Allergic reactions ranging from urticaria to anaphylaxis have occurred. Skin reactions ranging from mild eruptions to erythema multiforme, Stevens-Johnson syndrome, and toxic epidermal necrolysis have been reported rarely.

There have been reports of interstitial nephritis coincident with erythromycin use.

There have been reports of pancreatitis and convulsions.

There have been isolated reports of reversible hearing loss occurring chiefly in patients with renal insufficiency and in patients receiving high doses of erythromycin.

To report SUSPECTED ADVERSE EVENTS, contact Dr. Reddy’s Laboratories Inc, at 1-888-375-3784 or FDA at 1-800-FDA-1088 or http://www.fda.gov/medwatch for voluntary reporting of adverse reactions.

OVERDOSAGE

In case of overdosage, erythromycin should be discontinued. Overdosage should be handled with the prompt elimination of unabsorbed drug and all other appropriate measures.

Erythromycin is not removed by peritoneal dialysis or hemodialysis.

DOSAGE AND ADMINISTRATION

Erythromycin is well absorbed and may be given without regard to meals. Optimum blood levels are obtained in a fasting state (administration at least one half hour and preferably two hours before or after a meal); however, blood levels obtained upon administration of enteric-coated erythromycin products in the presence of food are still above minimal inhibitory concentrations (MICs) of most organisms for which erythromycin is indicated.

ADULTS: The usual dose is 250 mg every 6 hours taken one hour before meals. If twice-a-day dosage is desired, the recommended dose is 500 mg every 12 hours. Dosage may be increased up to 4 grams per day, according to the severity of the infection. Twice-a-day dosing is not recommended when doses larger than 1 gram daily are administered.
CHILDREN: Age, weight, and severity of the infection are important factors in determining the proper dosage. The usual dosage is 30 to 50 mg/kg/day in divided doses. For the treatment of more severe infections, this dose may be doubled.

Streptococcal infections

A therapeutic dosage of oral erythromycin should be administered for at least 10 days. For continuous prophylaxis against recurrences of streptococcal infections in persons with a history of rheumatic heart disease, the dose is 250 mg twice a day.

Primary syphilis

30 to 40 grams given in divided doses over a period of 10 to 15 days.

Intestinal amebiasis

250 mg four times daily for 10 to 14 days for adults; 30 to 50 mg/kg/day in divided doses for 10 to 14 days for children.

Legionnaires' disease

Although optimal doses have not been established, doses utilized in reported clinical data were those recommended above (1 to 4 grams daily in divided doses).

Urogenital infections during pregnancy due to Chlamydia trachomatis

Although the optimal dose and duration of therapy have not been established, the suggested treatment is erythromycin 500 mg, by mouth, 4 times a day on an empty stomach for at least 7 days. For women who cannot tolerate this regimen, a decreased dose of 250 mg, by mouth, 4 times a day should be used for at least 14 days.

For adults with uncomplicated urethral, endocervical, or rectal infections caused by Chlamydia trachomatis in whom tetracyclines are contraindicated or not tolerated: 500 mg, by mouth, 4 times a day for at least 7 days.

Pertussis

Although optimum dosage and duration of therapy have not been established, doses of erythromycin utilized in reported clinical studies were 40 to 50 mg/kg/day, given in divided doses for 5 to 14 days.

Nongonococcal urethritis due to Ureaplasma urealyticum

When tetracycline is contraindicated or not tolerated: 500 mg of erythromycin, orally, four times daily for at least 7 days.

Acute pelvic inflammatory disease due to N gonorrhoeae

500 mg IV of erythromycin lactobionate for injection, USP every 6 hours for 3 days followed by 250 mg of erythromycin, orally every six hours for 7 days.

HOW SUPPLIED

Each Erythromycin Delayed-Release Capsule, USP, 250 mg has an orange transparent body and orange opaque cap. The cap and body are imprinted with "250 mg" in black ink. Each capsule contains 250 mg erythromycin as enteric-coated pellets. The pellets are colored white.

The capsules are available as follows:

NDC 75907-076-01
Bottle of 100 capsules

STORAGE CONDITIONS

Store at controlled room temperature 15° C to 30° C (59° F to 86° F).

REFERENCES

1. Committee on Rheumatic Fever, Endocarditis, and Kawasaki Disease of the Council on Cardiovascular Disease in the Young, the American Heart Association: Prevention of Rheumatic Fever. Circulation. 78(4):1082-1086, October 1988.
2. Honein, M.A., et. al.: Infantile hypertrophic pyloric stenosis after pertussis prophylaxis with erythromycin: a case review and cohort study. The Lancet 1999;354 (9196): 2101-5.

RX Only

Distributed by: Dr. Reddy’s Laboratories Inc.
Princeton, NJ 08540

Product of Australia

Rev. 11/2023

PRINCIPAL DISPLAY PANEL - 250 mg Capsule Bottle Label

NDC 75907-076-01

Erythromycin
Delayed-Release
Capsules, USP

Each capsule contains 250 mg
erythromycin base as enteric-coated
pellets.

250 mg

Rx Only

Dr. Reddy's Laboratories, Inc

100 Capsules